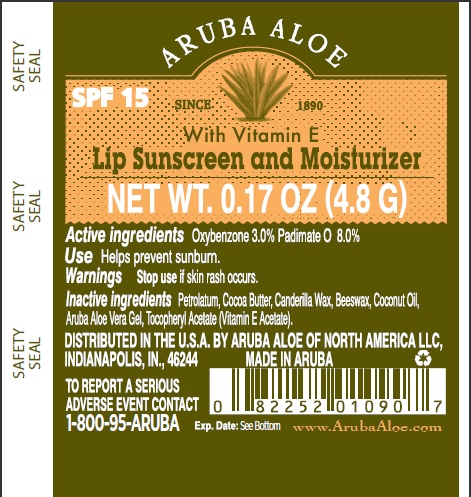 DRUG LABEL: Aruba Aloe Lip Sunscreen and Moisturizer
NDC: 53675-140 | Form: LIPSTICK
Manufacturer: Aruba Aloe Balm NV
Category: otc | Type: HUMAN OTC DRUG LABEL
Date: 20231106

ACTIVE INGREDIENTS: OXYBENZONE 3 g/100 g; PADIMATE O 8 g/100 g
INACTIVE INGREDIENTS: PETROLATUM; COCOA BUTTER; YELLOW WAX; COCONUT OIL; ALOE VERA LEAF; ACETATE ION

Aruba Aloe Lip Sunscreen and Moisturizer

PURPOSE

Lip Sunscreen and Moisturizer

DOSAGE AND ADMINISTRATION

Lip Sunscreen and Moisturizer

Active Ingredients

Oxybenzone 3.0% and Padimate O 8.0%

Use

Helps prevent sunburn

Warnings

Stop use if skin rash occurs

Inactive Ingredients

Petrolatum, Cocoa Butter, Canderila Wax, Beeswax, Coconut Oil, Aruba Aloe Vera Gel, Tocopheryl Acetate (Vitamin E Acetate).

DISTRIBUTED IN THE U.S.A. BY ARUBA ALOE OF NORTH AMERICA, LLC, INDIANAPOLIS, IN 46244

MADE IN ARUBA

TO REPORT A SERIOUS ADVERSE EVENT CONTACT 1-800-95-ARUBA

www.ArubaAloe.com